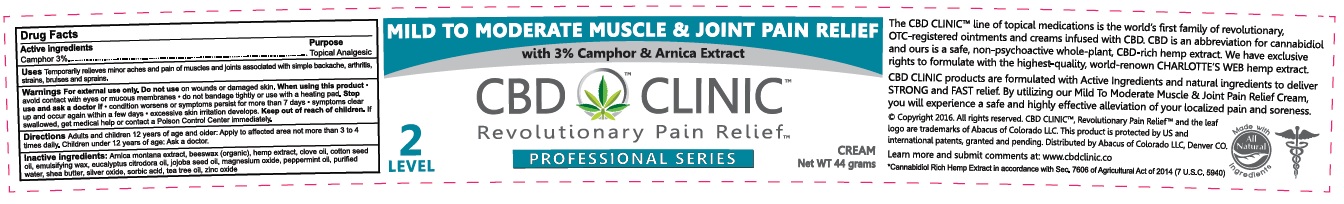 DRUG LABEL: CBD Clinic - Mild To Moderate Muscle and Joint Pain Relief
NDC: 24909-702 | Form: CREAM
Manufacturer: Aidance Skincare & Topical Solutions, LLC
Category: otc | Type: HUMAN OTC DRUG LABEL
Date: 20160714

ACTIVE INGREDIENTS: CAMPHOR (SYNTHETIC) 3 g/100 g
INACTIVE INGREDIENTS: ARNICA MONTANA; CETOSTEARYL ALCOHOL; CLOVE OIL; COTTONSEED OIL; EUCALYPTUS OIL; HEMP; JOJOBA OIL; MAGNESIUM OXIDE; PEPPERMINT OIL; POLYSORBATE 60; SHEA BUTTER; SILVER OXIDE; SORBIC ACID; TEA TREE OIL; WATER; WHITE WAX; ZINC OXIDE

Drug Facts

Active Ingredients

Camphor 3%

Purpose

Camphor - Topical Anesthetic

Uses

Temporarily relieves minor aches and pain of muscles and joints associated with simple backache, arthritis, strains, bruises and sprains.

Warnings

For external use only. Do not use on wounds or damaged skin. When using this product - avoid contact with eyes or mucous membranes - do not bandage tightly or use with heating pad. Stop use and ask a doctor if - condition worsens or symptoms persist for more than 7 days - symptoms clear up and occur again within a few days - excessive skin irritation develops.

Keep out of reach of children.

If swallowed, get medical help or contact a Poison Control Center immediately.

Directions

Adults and children 12 years of age and older: Apply to affected area not more than 3 to 4 times daily. Children under 12 years of age: Ask a doctor.

Inactive Ingredients

Arnica montana extract, beeswax (organic), hemp extract, clove oil, cotton seed oil, emulsifying wax, eucalyptus citrodora oil, jojoba seed oil, magnesium oxide, peppermint oil, purified water, shea butter, silver oxide, sorbic acid, tea tree oil, zinc oxide.

PRINCIPAL DISPLAY PANEL - 44g Label

MILD TO MODERATE MUSCLE & JOINT PAIN RELIEF

with 3% Camphor & Arnica Extract

CBD CLINIC

Revolutionary Pain Relief

Level 2 PROFESSIONAL SERIES Cream Net WT 44 grams